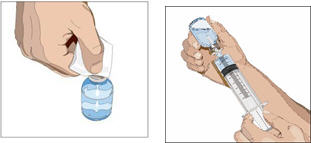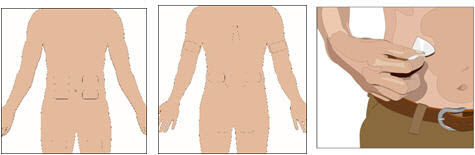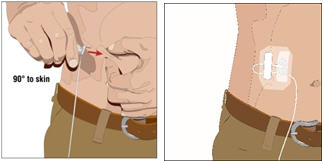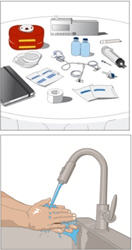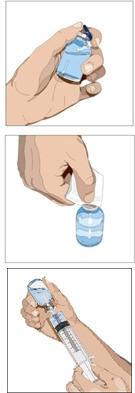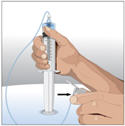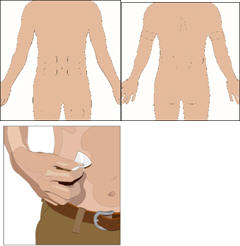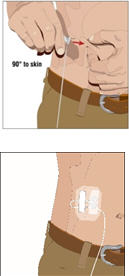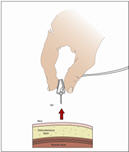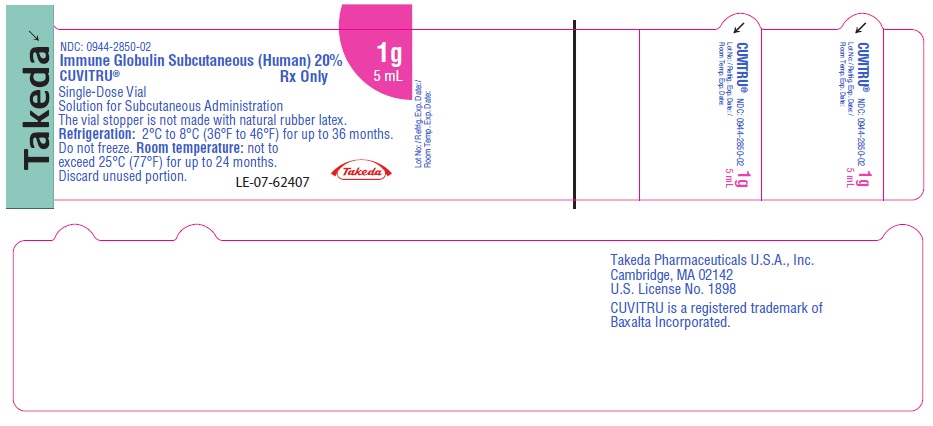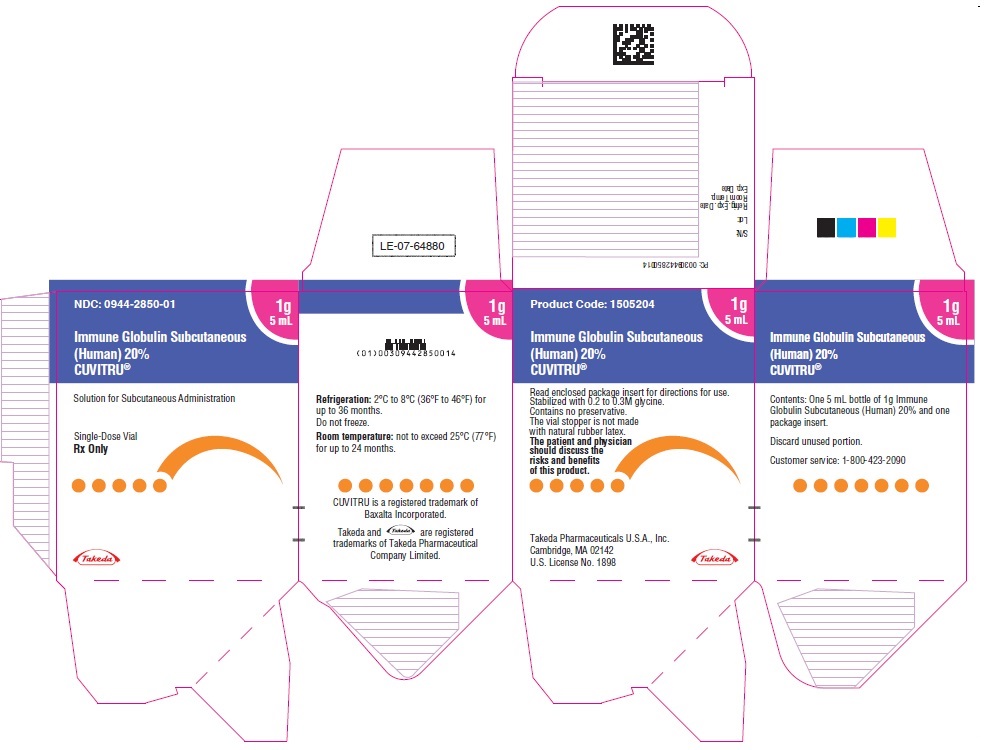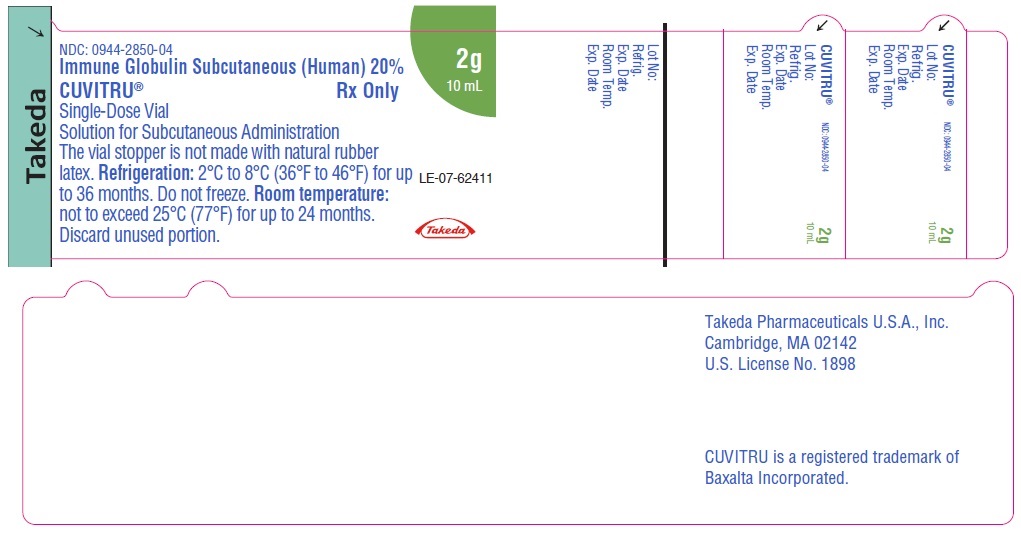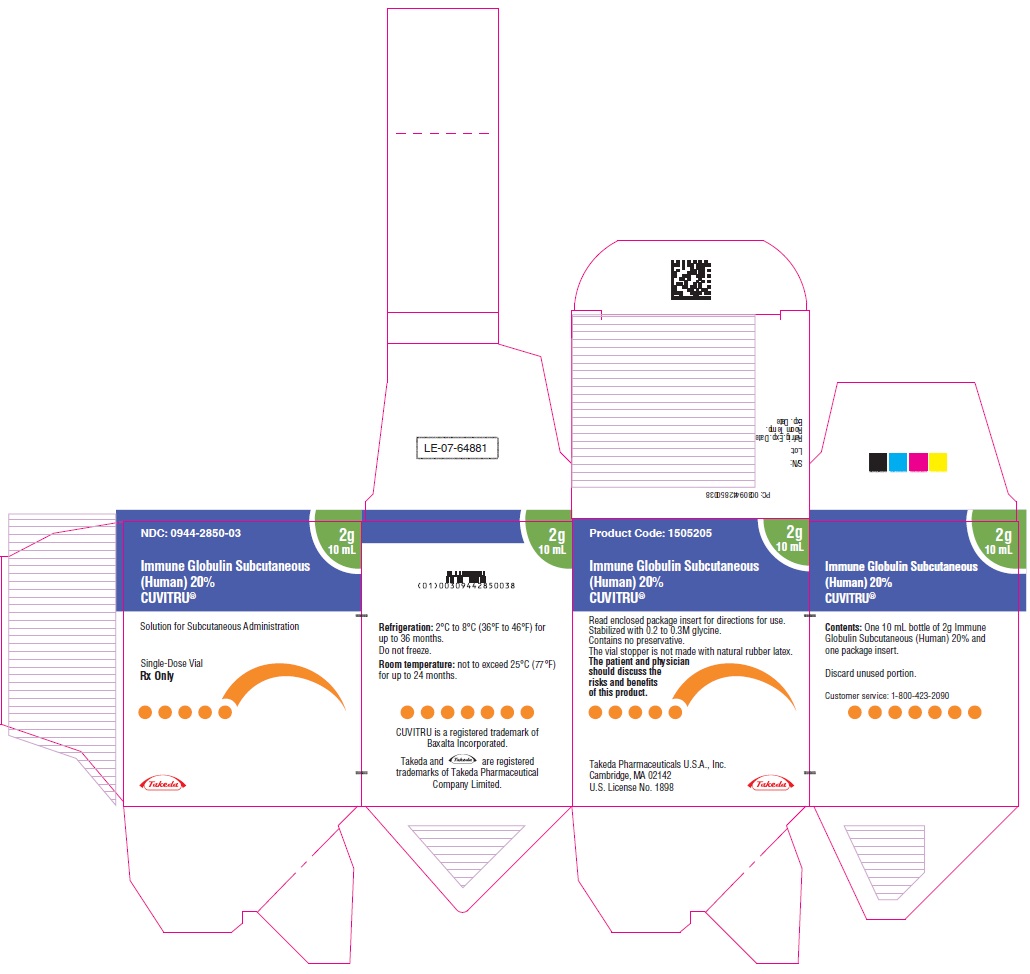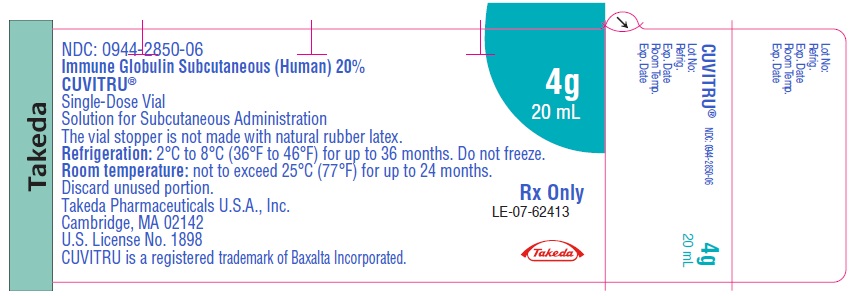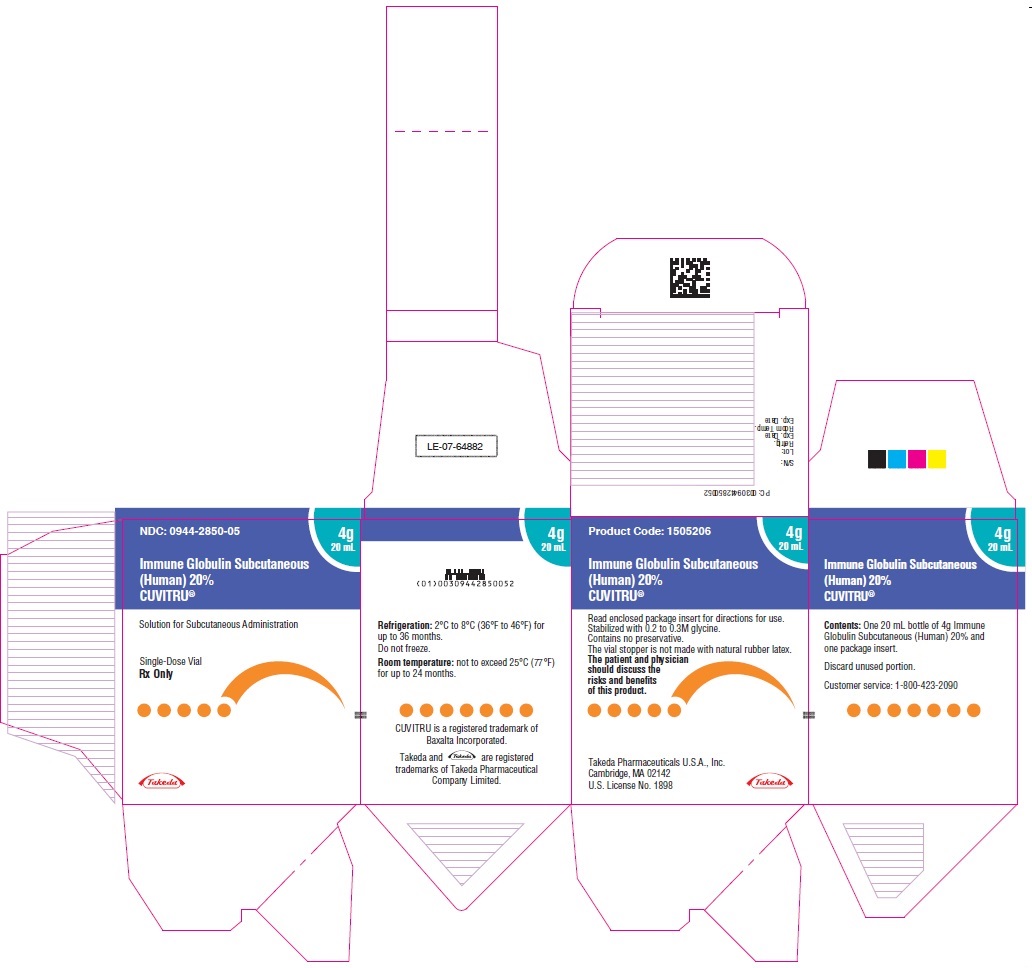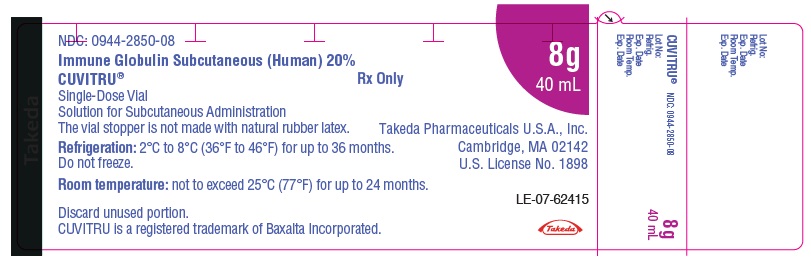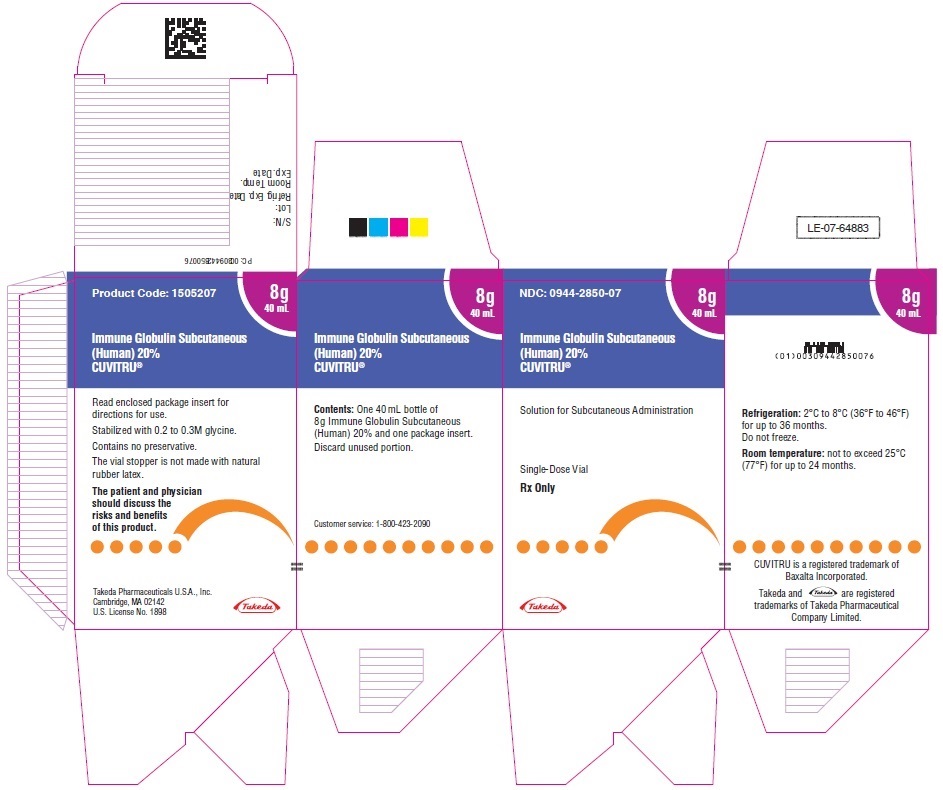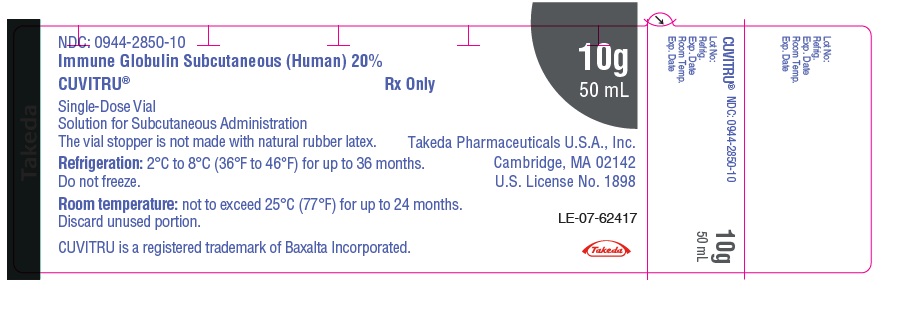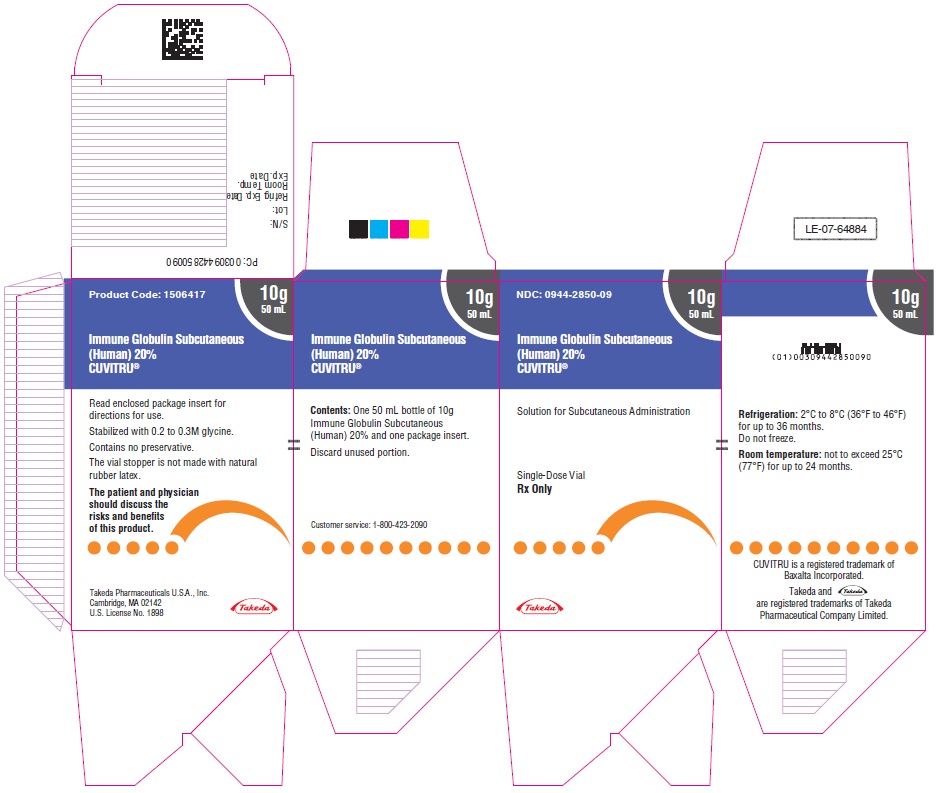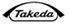 DRUG LABEL: CUVITRU
NDC: 0944-2850 | Form: INJECTION, SOLUTION
Manufacturer: Takeda Pharmaceuticals America, Inc.
Category: other | Type: PLASMA DERIVATIVE
Date: 20251125

ACTIVE INGREDIENTS: HUMAN IMMUNOGLOBULIN G 200 mg/1 mL
INACTIVE INGREDIENTS: GLYCINE

HIGHLIGHTS OF PRESCRIBING INFORMATION

These highlights do not include all the information needed to use CUVITRU® safely and effectively. See full prescribing information for CUVITRU.
CUVITRU®, Immune Globulin Subcutaneous (Human), 20% Solution
Initial U.S. Approval: 2016

WARNING: THROMBOSIS

See full prescribing information for complete boxed warning.

- Thrombosis may occur with immune globulin products, including CUVITRU. Risk factors may include: advanced age, prolonged immobilization, hypercoagulable conditions, history of venous or arterial thrombosis, use of estrogens, indwelling vascular catheters, hyperviscosity and cardiovascular risk factors.
- For patients at risk of thrombosis, administer CUVITRU at the minimum dose and infusion rate practicable. Ensure adequate hydration in patients before administration. Monitor for signs and symptoms of thrombosis and assess blood viscosity in patients at risk of hyperviscosity.

1 INDICATIONS AND USAGE

CUVITRU is an Immune Globulin Subcutaneous (Human), 20% solution indicated as replacement therapy for primary humoral immunodeficiency (PI) in adult and pediatric patients two years of age and older. (1)

2 DOSAGE AND ADMINISTRATION

For subcutaneous infusion only.

Administer at regular intervals from daily up to every two weeks (biweekly). (2.2)

Individualize dose based on the patient's pharmacokinetic and clinical response. (2.2)

Monitor serum IgG trough levels regularly to guide subsequent dose adjustments and dosing intervals as needed. (2.2)

Switching from Immune Globulin Intravenous (Human) treatment (IGIV) or adult patients switching from HYQVIA [Immune Globulin Infusion 10% (Human) with Recombinant Human Hyaluronidase]:

- Begin treatment one week after the patient's last IGIV or HYQVIA infusion. (2.2)
- Establish initial weekly dose by converting the monthly IGIV or HYQVIA dose into equivalent weekly dose and increasing it using a dose adjustment factor. (2.2)

Initial Weekly dose = | Previous IGIVor HYQVIA dose (in grams) × 1.30
 | No. of weeks between IGIV or HYQVIA doses

- Frequent dosing (2-7 times per week): Divide the calculated weekly dose by the desired number of times per week. (2.2)
- Biweekly dosing: Multiply the calculated weekly dose by 2. (2.2)
  Switching from Immune Globulin Subcutaneous (Human) treatment (IGSC):
- Weekly dose (in grams) should be the same as the weekly dose of prior IGSC treatment (in grams). (2.2)
- Frequent dosing (2-7 times per week): Divide the calculated weekly dose by the desired number of times per week. (2.2)
- Biweekly dosing: Multiply the calculated weekly dose by 2. (2.2)
  Infusion sites: up to 4 infusion sites simultaneously, with at least 4 inches between sites avoiding bony prominences. Rotate sites with each administration. (2.3)

3 DOSAGE FORMS AND STRENGTHS

200 mg/mL (20%) protein solution for subcutaneous infusion (3)

4 CONTRAINDICATIONS

- Anaphylactic or severe systemic hypersensitivity reactions to subcutaneous administration of Immune Globulin (Human). (4)
- IgA deficient patients with antibodies against IgA and a history of hypersensitivity. (4)

5 WARNINGS AND PRECAUTIONS

- IgA deficient patients with antibodies to IgA are at greater risk of developing severe hypersensitivity and anaphylactic reaction. (5.1)
- Monitor renal function, including blood urea nitrogen, serum creatinine, and urine output in patients at risk of acute renal failure. (5.2)
- Thrombosis may occur. Monitor for signs and symptoms of thrombosis and assess blood viscosity for those at risk for hyperviscosity. (5.3)
- Aseptic Meningitis Syndrome (AMS) can occur. (5.4)
- Monitor for clinical signs and symptoms of hemolysis. (5.5)
- Monitor patients for pulmonary adverse reactions (transfusion-related acute lung injury, TRALI). (5.6)
- Product is made from human blood, it may carry a risk of transmitting infectious agents, e.g., viruses, the variant Creutzfeldt-Jakob disease (vCJD) agent, and theoretically, the Creutzfeldt-Jakob disease agent. (5.7)

6 ADVERSE REACTIONS

The most common adverse reactions observed in ≥5% of patients were: local adverse reactions, systemic adverse reactions including headache, nausea, fatigue, diarrhea, and vomiting. (6.1)

To report SUSPECTED ADVERSE REACTIONS, contact Takeda Pharmaceuticals U.S.A., Inc. at 1-877-TAKEDA-7 (1-877-825-3327) or FDA at 1-800-FDA-1088 or www.fda.gov/medwatch.

7 DRUG INTERACTIONS

Passive transfer of antibodies may transiently interfere with the immune responses to live virus vaccines, such as measles, mumps, rubella, and varicella. (7)

FULL PRESCRIBING INFORMATION

WARNING: THROMBOSIS

- Thrombosis may occur with immune globulin products, including CUVITRU. Risk factors may include advanced age, prolonged immobilization, hypercoagulable conditions, history of venous or arterial thrombosis, use of estrogens, indwelling vascular catheters, hyperviscosity and cardiovascular risk factors.
- For patients at risk of thrombosis, administer CUVITRU at the minimum dose and infusion rate practicable. Ensure adequate hydration in patients before administration. Monitor for signs and symptoms of thrombosis and assess blood viscosity in patients at risk of hyperviscosity.

1 INDICATIONS AND USAGE

CUVITRU is an Immune Globulin Subcutaneous (Human) (IGSC), 20% Solution indicated as replacement therapy for primary humoral immunodeficiency (PI) in adult and pediatric patients two years of age and older. This includes, but is not limited to, common variable immunodeficiency (CVID), X-linked agammaglobulinemia, congenital agammaglobulinemia, Wiskott-Aldrich syndrome, and severe combined immunodeficiencies^1,2.

2 DOSAGE AND ADMINISTRATION

For subcutaneous administration only. Do not administer intravenously or intramuscularly.

2.1 Preparation and Handling

- Inspect the drug product visually for particulate matter and discoloration prior to administration. CUVITRU is a clear and colorless or pale yellow or light brown solution and clear of particulate matter. Do not use if the solution is cloudy, turbid, or if it contains particulates.
- Do not mix CUVITRU with other products.
- Do not shake.
- Do not dilute.
- CUVITRU comes in a single-dose vial. Any vial that has been entered should be used promptly. Partially used vials should be discarded. CUVITRU contains no preservative.
- Record the name and lot number of the product in the recipient's records.

2.2 Dose

- CUVITRU can be administered at regular intervals from daily up to every two weeks (biweekly).
- Individualize the dose based on the patient's pharmacokinetic and clinical response.
- Monitor serum IgG trough levels regularly to guide subsequent dose adjustments and dosing intervals as needed (see Dose Adjustment).

For patients switching from Immune Globulin Intravenous (Human) treatment (IGIV) or adult patients switching from HYQVIA [Immune Globulin Infusion 10% (Human) with Recombinant Human Hyaluronidase]:

- Begin treatment with CUVITRU one week after the patient's last IGIV or HYQVIA infusion.
- Establish the initial weekly dose by converting the monthly IGIV or HYQVIA dose into an equivalent weekly dose and increasing it using a dose adjustment factor.
- To calculate the initial weekly dose, divide the previous IGIV or HYQVIA dose in grams by the number of weeks between intravenous doses; then multiply this dose by the dose adjustment factor of 1.30.
  Initial Weekly dose = | Previous IGIV or HYQVIA dose (in grams) | × 1.30
   | Number of weeks between IGIV or HYQVIA doses
- To convert the dose (in grams) to milliliters (mL), multiply the calculated dose (in grams) by 5.
- Doses divided over the course of a week, or once weekly, or biweekly, achieve similar exposure when administered regularly at steady-state.
- To determine the dose for alternative regular dosing intervals:
  ‒ Frequent dosing (2-7 times per week): Divide the calculated weekly dose by the desired number of times per week.
  ‒ Biweekly dosing: Multiply the calculated weekly dose by 2.

To guide dose adjustments, see section Dose Adjustments (Table 1).

For patients switching from Immune Globulin Subcutaneous (Human) treatment (IGSC):

- The weekly dose of CUVITRU (in grams) is recommended to be the same as the weekly dose of prior IGSC treatment (in grams).
- Doses divided over the course of a week, once weekly, or biweekly, achieve similar exposure when administered regularly at steady-state.
- To determine the dose for alternative regular dosing intervals:
  ‒ Frequent dosing (2-7 times per week): Divide the calculated weekly dose by the desired number of times per week.
  ‒ Biweekly dosing: Multiply the calculated weekly dose by 2.
- To convert the dose (in grams) to milliliters (mL), multiply the calculated dose (in grams) by 5.

To guide dose adjustments, see section Dose Adjustments (Table 1).

For patients at risk for measles exposure:

- If a patient has been exposed to measles, it may be prudent to administer a dose of Immune Globulin Intravenous as soon as possible and within 6 days of exposure. A dose of 400 mg/kg should provide a serum level >240 mIU/mL of measles antibodies for at least two weeks.
- If a patient is at risk of future measles exposure and receives a dose of CUVITRU of less than 230 mg/kg subcutaneously per week, the dose should be increased to at least 230 mg/kg per week, or the weekly equivalent of 230 mg/kg for dosing intervals other than weekly.

Dose Adjustment:

To guide dose adjustment, calculate the difference between the patient's target serum IgG trough level and the IgG trough level during subcutaneous treatment. Find this difference in Table 1 and the corresponding amount (in mL) by which to increase (or decrease) the weekly/biweekly dose based on the patient's body weight. If the difference between measured and target trough levels is less than 100 milligram/dL, then no adjustment is necessary. However, the patient's clinical response should be the primary consideration in dose adjustment.

Table 1 Change in Volume to Be Administered Weekly/Biweekly for Intended IgG Trough Level Change [Derived using a linear approximation of trough levels and weekly dose per kg body mass with a slope of 52.1 kg/dL.]
 |  | Body Weight
Difference from Target Serum IgG Trough Levels | Dosing Frequency | 30 kg | 50 kg | 70 kg | 90 kg | 110 kg
100 mg/dL | Weekly | 3 mL | 5 mL | 7 mL | 9 mL | 11 mL
 | Biweekly | 6 mL | 10 mL | 13 mL | 17 mL | 21 mL
200 mg/dL | Weekly | 6 mL | 10 mL | 13 mL | 17 mL | 21 mL
 | Biweekly | 12 mL | 19 mL | 27 mL | 35 mL | 42 mL
300 mg/dL | Weekly | 9 mL | 14 mL | 20 mL | 26 mL | 32 mL
 | Biweekly | 17 mL | 29 mL | 40 mL | 52 mL | 63 mL

Example 1: A patient with a body weight of 70 kg who is on a weekly treatment has a measured IgG trough level of 600 milligrams/dL, and the target trough level is 800 milligrams/dL. The desired target trough level difference is 200 milligrams/dL (800 milligrams/dL minus 600 milligrams/dL). The weekly dose of CUVITRU should be increased by 13 mL.

Example 2: A patient with a body weight of 50 kg who is on a biweekly treatment has a measured IgG trough of 900 milligrams/dL, and the target trough level is 700 milligrams/dL. The desired target trough level difference is 200 milligrams/dL (900 milligrams/dL minus 700 milligrams/dL). The biweekly dose of CUVITRU should be decreased by 19 mL.

2.3 Administration

Table 2 Infusion Volume and Rate [If the initial infusions are well tolerated then subsequent infusions can begin at the maximum tolerated rate]
Infusion Parameters | First 2 Infusions |  | Subsequent Infusions
Infusion Parameters | Patients <40 kg | Patients ≥40 kg | Patients <40 kg | Patients ≥40 kg
Volume (mL/site) | ≤20 | ≤60 | ≤60
Rate (mL/hr/site) | 10 - 20 |  | ≤60

Selection of Infusion Site: Suggested areas for subcutaneous infusion of CUVITRU are abdomen, thighs, upper arms, or lateral hip. CUVITRU may be infused into multiple infusion sites. Use up to 4 sites simultaneously. Infusion sites should be at least four inches apart, avoiding bony prominences. Rotate sites with each administration.

Volume per Site: To calculate the number of sites to be used, divide the total volume to be infused by the maximum volume/site (up to 60 mL/site) to be infused. Simultaneous subcutaneous infusion at multiple sites can be facilitated by use of a multi-needle administration set.

Infusion rate: For the first two infusions of CUVITRU, the recommended infusion rate is 10-20 mL/hr/site. For subsequent infusions, the infusion rate may be increased to 60 mL/hr/site as tolerated (e.g., 60 mL/hr/site × 2 sites = 120 mL/hr). For patients utilizing 4 infusion sites, the maximum infusion rate for all sites combined is 240 mL/hr.

Instructions for Administration:

Use aseptic technique when preparing and administering CUVITRU for infusion.

1. Inspect the vials: Inspect for clarity, color, and expiration date(s) [see Dosage and Administration (2.1)].
2. Prepare for infusion:
  - Gather supplies: CUVITRU vial(s), ancillary supplies, sharps container and infusion pump.
  - Prepare a clean work area.
  - Wash hands.
3. Prepare the CUVITRU:
  - Wipe each stopper with a sterile alcohol wipe and allow to dry.
  - Transfer into syringe(s), preferably using a vented spike.
  - Start the infusion promptly after drawing CUVITRU into the syringe. It is suggested to complete the administration within 2 hours due to the potential formation of particles caused by siliconized syringes.
4. Prepare the infusion pump and tubing:
  - Follow manufacturer directions for priming the tubing and pump usage.
  - Attach the syringe filled with CUVITRU to the needle set.
  - Prime the needle set up to the needle hub.
5. Prepare the infusion site(s):
  - Potential sites for infusion include the abdomen, thighs, upper arms, or lateral hip.
  - Avoid: bony areas, visible blood vessels, scars and any areas of inflammation (irritation) or infection.
  - The number and location of infusion sites depends on the volume of the total dose.
  - Infusion sites should be at least 4 inches apart.
  - Rotate sites of the body between successive infusions.
  - Cleanse the infusion site(s) with a sterile alcohol wipe beginning at the center of each infusion site and moving outward in a circular motion. Allow the infusion site(s) to dry.
6. Insert and secure the subcutaneous needle set:
  - Pinch at least one inch of skin between two fingers. Insert the needle at a 90-degree angle into the subcutaneous tissue and secure the needle with sterile tape.
  - If more than one site is used, repeat steps.
  - Secure the needle in place with a sterile protective dressing.
7. Start the infusion of CUVITRU based on prescriber's order:
  Follow the manufacturer's instructions to turn on the infusion pump.
8. Remove subcutaneous needle(s) from the infusion site(s):
  After the infusion is complete, remove the needle set and cover with a protective dressing. Discard any partially used vial(s) and disposable supplies in accordance with local requirements.
9. Document the infusion:
  Remove the peel-off label from each vial of CUVITRU used and affix to the patient's treatment record or infusion log. In addition, record the time, date, dose, infusion site location and any reactions after each infusion.

For self-administration, provide the patient with instructions and training for infusion in the home or other appropriate setting.

3 DOSAGE FORMS AND STRENGTHS

CUVITRU is a 200 mg/mL (20%) protein solution for subcutaneous infusion.

4 CONTRAINDICATIONS

- CUVITRU is contraindicated in patients who have had an anaphylactic or severe systemic hypersensitivity reaction to the subcutaneous administration of human immune globulin.
- CUVITRU is contraindicated in IgA-deficient patients with antibodies against IgA and a history of hypersensitivity to human immune globulin treatment.

5 WARNINGS AND PRECAUTIONS

5.1 Hypersensitivity

Severe hypersensitivity reactions may occur, even in patients who had tolerated previous treatment with human immune globulin. If a hypersensitivity reaction occurs, discontinue CUVITRU infusion immediately and institute appropriate treatment.

CUVITRU contains trace amounts of IgA (average concentration of 80 mcg/mL). Patients with known antibodies to IgA have a greater risk of developing potentially severe hypersensitivity reactions, including anaphylaxis, with administration of CUVITRU.

5.2 Renal Dysfunction/Failure

Acute renal dysfunction/failure, acute tubular necrosis, proximal tubular nephropathy, osmotic nephrosis, and death may occur upon use of immune globulin treatment, especially those containing sucrose^3,4. CUVITRU does not contain sucrose. Ensure that patients are not volume depleted prior to the initiation of infusion of CUVITRU. In patients who are at risk of developing renal dysfunction because of pre-existing renal insufficiency or predisposition to acute renal failure (such as diabetes mellitus, age greater than 65, volume depletion, sepsis, paraproteinemia, or patients receiving known nephrotoxic drugs), monitor renal function and consider lower, more frequent dosing[see Dosage and Administration (2.1)].

Periodic monitoring of renal function and urine output is particularly important in patients predisposed to be at increased risk for developing acute renal failure. Assess renal function, including measurement of blood urea nitrogen (BUN) and serum creatinine, before the initial infusion of CUVITRU and again at appropriate intervals thereafter. If renal function deteriorates, consider discontinuation of CUVITRU [see Dosage and Administration (2.3)].

5.3 Thrombosis

Thrombosis may occur following treatment with immune globulin products.^5,6 Risk factors may include advanced age, prolonged immobilization, hypercoagulable conditions, history of venous or arterial thrombosis, use of estrogens, indwelling central vascular catheters, hyperviscosity, and cardiovascular risk factors. Thrombosis may occur in the absence of known risk factors.

Consider baseline assessment of blood viscosity in patients at risk for hyperviscosity, including those with cryoglobulins, fasting chylomicronemia/markedly high triacylglycerols (triglycerides), or monoclonal gammopathies. For patients at risk of thrombosis, administer CUVITRU at the minimum dose and infusion rate practicable. Ensure adequate hydration in patients before administration. Monitor for signs and symptoms of thrombosis and assess blood viscosity in patients at risk for hyperviscosity [see Boxed Warning, Dosage and Administration (2.1), Patient Counseling Information (17)].

5.4 Aseptic Meningitis Syndrome (AMS)

AMS has been reported with the use of immune globulin, including CUVITRU [See Postmarketing Experience (6.2)]. The syndrome usually begins within several hours to two days following immune globulin treatment. AMS may occur more frequently in female patients.

AMS is characterized by the following signs and symptoms: severe headache, nuchal rigidity, drowsiness, fever, photophobia, painful eye movements, nausea and vomiting [see Patient Counseling Information (17)]. Cerebrospinal fluid (CSF) studies frequently reveal pleocytosis up to several thousand cells per mm^3, predominantly from the granulocytic series, and elevated protein levels up to several hundred milligram/dL, but negative culture results. Conduct a thorough neurological examination, including CSF studies, on patients exhibiting such signs and symptoms, to rule out other causes of meningitis. Discontinuation of treatment has resulted in remission of AMS within several days without sequelae.

5.5 Hemolysis

CUVITRU can contain blood group antibodies that may act as hemolysins and induce in vivo coating of red blood cells (RBC) with immune globulin. This may cause a positive direct antiglobulin test [DAT (Coombs test)]^7,8. Delayed hemolytic anemia can develop subsequent to CUVITRU therapy due to enhanced RBC sequestration; acute hemolysis, consistent with intravascular hemolysis, can occur^7-11.

The following risk factors may be related to the development of hemolysis: high doses (e.g., ≥2 grams/kg, single administration or divided over several days) and non-O blood group^(7, 11). Underlying inflammatory state in an individual patient may increase the risk of hemolysis^7 but its role is uncertain^10,12.

Monitor patients for clinical signs and symptoms of hemolysis, particularly patients with risk factors noted above. Consider appropriate laboratory testing in higher risk patients, including measurement of hemoglobin or hematocrit prior to infusion and within approximately 36 to 96 hours post infusion.

5.6 Transfusion-Related Acute Lung Injury (TRALI)

Non-cardiogenic pulmonary edema (TRALI) has been reported in patients following treatment with immune globulin products. TRALI is characterized by severe respiratory distress, pulmonary edema, hypoxemia, normal left ventricular function, and fever. Symptoms typically occur within 1 to 6 hours after treatment.

Monitor patients for pulmonary adverse reactions. If TRALI is suspected, perform appropriate tests for the presence of anti-neutrophil and anti-HLA antibodies in both the product and patient serum. TRALI may be managed using oxygen therapy with adequate ventilatory support.

5.7 Transmissible Infectious Agents

Because CUVITRU is made from human blood, it may carry a risk of transmitting infectious agents, e.g., viruses, the variant Creutzfeldt-Jakob disease (vCJD) agent, and theoretically, the Creutzfeldt-Jakob disease agent. This also applies to unknown or emerging viruses and other pathogens. No confirmed cases of viral transmission or vCJD have been associated with CUVITRU.

All infections thought by a physician to possibly have been transmitted by this product should be reported by the physician or other healthcare provider to Takeda Pharmaceuticals U.S.A., Inc., at 1-877-TAKEDA-7 (1-877-825-3327).

5.8 Monitoring: Laboratory Tests

- Periodic monitoring of renal function and urine output is particularly important in patients predisposed to be at increased risk of developing acute renal failure. Assess renal function, including measurement of BUN and serum creatinine, before the initial infusion of CUVITRU and at appropriate intervals thereafter.
- Consider baseline assessment of blood viscosity in patients at risk for hyperviscosity, including those with cryoglobulins, fasting chylomicronemia/markedly high triacylglycerols (triglycerides), or monoclonal gammopathies, because of the potentially increased risk of thrombosis^3,5.
- If signs and/or symptoms of hemolysis are present after an infusion of CUVITRU, perform appropriate laboratory testing for confirmation.
- If TRALI is suspected, perform appropriate tests for the presence of anti-neutrophil antibodies and anti-HLA antibodies in both the product and patient's serum.

5.9 Interference with Laboratory Tests

- After infusion of IgG, the transitory rise of the various passively transferred antibodies in the patient's blood may yield false positive serological test results, with the potential for misleading interpretation. Passive transmission of antibodies to erythrocyte antigens (e.g., A, B, and D) may cause a positive direct or indirect antiglobulin (Coombs') test.
- Administration of CUVITRU can lead to false positive readings in assays that depend on detection of beta-D-glucans for diagnosis of fungal infections; this may persist during the weeks following infusion of the product.

6 ADVERSE REACTIONS

The most common adverse reactions observed in ≥5% of subjects were: local adverse reactions, systemic adverse reactions including headache, nausea, fatigue, diarrhea, and vomiting.

6.1 Clinical Trials Experience

Because clinical trials are conducted under widely varying conditions, adverse reaction rates observed in the clinical trials of a drug cannot be directly compared to rates in the clinical trials of another drug and may not reflect the rates observed in clinical practice.

CUVITRU was administered subcutaneously in two prospective, open-label, non-controlled, multicenter studies to evaluate efficacy, safety, tolerability, and pharmacokinetics in subjects with primary immunodeficiency (PI). One study was performed in North America and the other was performed in Europe.

North American Study

In a clinical study conducted in North America, 67 out of 74 subjects treated with CUVITRU completed the study including 20/21 subjects aged 2 to <16 years old. Of the 7 subjects that discontinued treatment with CUVITRU, one subject withdrew due to fatigue (assessed as not related), 1 subject withdrew because of non-compliance, and 5 subjects withdrew for personal reasons.

A total of 4,327 CUVITRU infusions were administered during the clinical study. No serious adverse reactions occurred during treatment with CUVITRU; 278 non-serious adverse reactions occurred at a rate per infusion of 0.06. Among the 4,327 CUVITRU infusions, 99.3% (276/278) of adverse reactions were mild or moderate and transient in nature. Of the 278 non-serious adverse reactions (excluding infections), 83% (231/278) were rated as mild, 16% (45/278) were rated as moderate, and 1% (2/278, hemoptysis and abdominal pain) were severe.

Adverse reactions occurring in ≥5% of subjects (defined as adverse events occurring during or within 72 hours of infusion or any causally related event occurring within the study period) are shown in Table 3. No subject discontinued treatment due to local adverse reactions.

Table 3 Adverse Reactions [Excluding infections] in ≥5% of Subjects Associated with Infusions of CUVITRU
Adverse Reactions | By Subject N (%) [Number and percentages of affected subjects] (N=74 Subjects) | By Infusion N (Rate) [Rate = Total number of adverse reactions divided by the total number of infusions under treatment] (N=4,327 infusions)
Local Adverse Reactions | 23 (31.1%) | 96 (0.022)
Systemic Adverse Reactions | 41 (55.4%) | 182 (0.042)
Headache | 10 (13.5%) | 50 (0.012)
Nausea | 9 (12.2%) | 16 (0.004)
Fatigue | 6 (8.1%) | 9 (0.002)
Diarrhea | 5 (6.8%) | 5 (0.001)
Vomiting | 4 (5.4%) | 5 (0.001)

Systemic adverse reactions to immune globulin intravenous in part 1 of the study occurred at a rate of 0.302 relative to a rate of 0.042 during treatment with CUVITRU. The CUVITRU systemic adverse reaction rate was approximately 7-fold lower than the immune globulin intravenous rate.

Local Adverse Reactions: The most frequent local adverse reactions are listed by frequency in Table 4. Of the total 96 local adverse reactions, 100% were either mild (92.5%) or moderate (7.5%) in severity. No severe local adverse reactions were reported. During the clinical study, no local adverse reactions were observed in 68.9% (51/74) of subjects and in 98.2% (4,247/4,327) of infusions. The overall rate of local adverse reactions (excluding infections) during the clinical study was 0.022 (0.021 mild and 0.002 moderate). The rate of local adverse reactions was not associated with increased rate of infusion or volume per site.

Table 4 Most Frequent Local Adverse Reactions Reported in ≥5% of Subjects
Events | Total Number of Adverse Reactions |  | By Subject N (%) [Number and percentages of affected subjects] (N =74 Subjects) | By Infusion N (Rate) [Rate= Total number of adverse reactions divided by the total number of infusions under treatment] (N=4,327 infusions)
 | Mild | Moderate
Pain | 33 | 3 | 15 (20.3%) | 36 (0.008)
Erythema | 22 | 1 | 8 (10.8%) | 23 (0.005)
Pruritus | 7 | 1 | 4 (5.4%) | 8 (0.002)

European Study

Efficacy and safety during treatment with CUVITRU were evaluated in 48 subjects in a clinical trial in Europe. CUVITRU was administered for a median treatment duration of 358 days (range: 127.0-399 days) and a mean (± SD) of 347.4 ± 47.9 days. CUVITRU treatment: 45/48 subjects treated with CUVITRU completed the study, including 23/25 subjects aged 2 to <18 years old.

A total of 2,349 CUVITRU infusions were administered during this clinical study. No serious adverse reactions occurred during treatment with CUVITRU. In total, 176 local adverse reactions and 205 systemic adverse reactions were reported (adverse reaction defined as adverse events occurring during or within 72 hours of infusion or any causally related event occurring within the study period), excluding infections. Of the 205 systemic reactions, the majority (134) were mild, 70 were moderate and one event was severe (headache, assessed as temporally associated, not causally related). The rate of systemic adverse reactions (excluding infections) during treatment with CUVITRU was 0.087, and the rate of related systemic AEs (excluding infections) per infusion was 0.032. During treatment with IGIV 10% in study part 1, the rate of related systemic AEs (excluding infections) was 0.173 events per infusion. The CUVITRU related systemic adverse event rate was approximately 5-fold lower than the immune globulin intravenous rate.

Table 5 EU Study: Adverse Reactions [Causally Related and/or Temporally Associated (Within 72 Hour) AEs (Excluding Infections)] in ≥5% of Subjects Associated with Infusions of CUVITRU
Adverse Reactions | By Subject N (%) [Total number of affected subjects divided by the total number of subjects under treatment] (N=48 Subjects) | By Infusion N (Rate) [Total number of AEs divided by the total number of infusions under treatment] (N=2,349 infusions)
Local Adverse Reactions | 18 (37.5%) | 176 (0.075)
Systemic Adverse Reactions | 33 (68.8%) | 205 (0.087)
Headache | 14 (29.2%) | 59 (0.025)
Diarrhea | 9 (18.8%) | 58 (0.025)
Cough | 5 (10.4%) | 7 (0.003)
Fatigue | 6 (12.5) | 8 (0.003)
Arthralgia | 3 (6.3%) | 5 (0.002)
Oropharyngeal pain | 3 (6.3%) | 3 (0.001)

Local Adverse Reactions: Among the 176 local adverse reactions in total (adverse reaction defined as adverse events occurring during or within 72 hours of infusion or any causally related event occurring within the study period), none was severe. In total, 175 adverse reactions (99.4%) were mild, and 1 adverse reaction (0.6%) was moderate. The overall rate of local adverse reactions was 0.075 per infusion. The most common reactions (by subject) were infusion site pain, infusion site erythema and infusion site pruritus.

Table 6 EU Study: Most Frequent Local Adverse Reactions Reported in ≥5% of Subjects
Events | Total Number of Adverse Reactions |  | By Subject N (%) [Number and percentages of affected subjects] (N =48 Subjects) | By Infusion N (Rate) [Rate= Total number of adverse reactions divided by the total number of infusions under treatment] (N=2,349 infusions)
 | Mild | Moderate
Pain | 34 | 0 | 10 (20.8%) | 34 (0.014)
Erythema | 54 | 0 | 10 (20.8%) | 54 (0.023)
Pruritus | 30 | 0 | 7 (14.6%) | 30 (0.013)
Swelling | 46 | 0 | 4 (8.3%) | 46 (0.020)

6.2 Postmarketing Experience

Because postmarketing reporting of adverse reactions is voluntary and from a population of uncertain size, it is not always possible to reliably estimate the frequency of these reactions or establish a causal relationship to product exposure.

In addition to the adverse reactions listed above in clinical trials, the following adverse reactions have been reported in the postmarketing experience:

Infections and Infestations: Aseptic meningitis

Postmarketing Experience of Immune Globulin Products

The following adverse reactions have been identified and reported during the postmarketing use of immune globulin products administered subcutaneously:

Immune system disorders | Anaphylactic reaction
Cardiac disorders | Tachycardia
Nervous system disorders | Tremor and paresthesia
Respiratory, Thoracic and Mediastinal disorders | Dyspnea and laryngospasm
General disorders and administration site conditions | Injection site reaction (such as induration and warmth) and chest discomfort

7 DRUG INTERACTIONS

Passive transfer of antibodies may transiently impair the immune responses to live attenuated virus vaccines such as mumps, rubella and varicella for up to 6 months and for a year or more to measles (rubeola). Inform the immunizing physician of recent therapy with CUVITRU so that appropriate precautions can be taken [see Patient Counseling Information (17)].

8 USE IN SPECIFIC POPULATIONS

8.1 Pregnancy

Risk Summary

No human data are available to indicate the presence or absence of drug-associated risk. Animal reproduction studies have not been conducted with CUVITRU. It is also not known whether CUVITRU can cause fetal harm when administered to a pregnant woman or can affect reproductive capacity. Immune globulins cross the placenta from maternal circulation increasingly after 30 weeks of gestation. CUVITRU should be given to a pregnant woman only if clearly indicated. In the U.S. general population, the estimated background risk of major birth defects and miscarriage in clinically recognized pregnancies is 2-4% and 15-20%, respectively.

8.2 Lactation

Risk Summary

No human data are available to indicate the presence or absence of drug-associated risk. The developmental and health benefits of breastfeeding should be considered along with the mother's clinical need for CUVITRU and any potential adverse effects on the breastfed infant from CUVITRU or from the underlying maternal condition.

8.4 Pediatric Use

CUVITRU was evaluated in 21 pediatric subjects with PI (2 to 16 years of age) in a multicenter clinical study. The safety and efficacy profiles were similar to adult subjects. No pediatric-specific dose requirements were necessary to achieve the desired serum IgG levels.

Safety and effectiveness of CUVITRU has not been evaluated in neonates or infants <2 years old.

8.5 Geriatric Use

CUVITRU was evaluated in 9 subjects over the age of 65 years in a multicenter clinical study. No differences in safety or efficacy were observed for this group when compared to the rest of the study population.

Monitor patients who are at an increased risk for developing renal failure or thrombotic events. Do not exceed the recommended dose, and infuse at the minimum infusion rate practicable [see Boxed Warning, Warnings and Precautions (5.2, 5.4), Dosage and Administration (2.3)].

11 DESCRIPTION

CUVITRU is a ready-for-use, sterile, liquid preparation of highly purified and concentrated immunoglobulin G (IgG) antibodies. The distribution of the IgG subclasses is similar to that of normal plasma. The Fc and Fab functions are maintained in CUVITRU.

CUVITRU has a purity ≥98% IgG and a pH of 4.6 to 5.1. The osmolality is 280-292 milli-osmoles per kilogram. CUVITRU contains 200 milligram/mL protein. The average immunoglobulin A (IgA) concentration is 80 mcg/mL. CUVITRU contains a broad spectrum of IgG antibodies against bacterial and viral agents. Glycine (0.25M) serves as a stabilizing and buffering agent, and there are no added sugars, sodium or preservatives.

CUVITRU is manufactured from large pools of human plasma. IgG preparations are purified from plasma pools using a modified Cohn-Oncley cold ethanol fractionation process, as well as cation and anion exchange chromatography.

Screening against potentially infectious agents begins with the donor selection process and continues throughout plasma collection and plasma preparation. Each individual plasma donation used in the manufacture of CUVITRU is collected only at FDA approved blood establishments and is tested by FDA licensed serological tests for Hepatitis B Surface Antigen (HBsAg), and for antibodies to Human Immunodeficiency Virus (HIV-1/HIV-2) and Hepatitis C Virus (HCV) in accordance with U.S. regulatory requirements. As an additional safety measure, mini-pools of the plasma are tested for the presence of HIV-1 and HCV by FDA licensed Nucleic Acid Testing (NAT) and found to be negative.

To further improve the margin of safety, validated virus inactivation/removal steps have been integrated into the manufacturing and formulation processes, namely solvent/detergent (S/D) treatment^13, 35 nm nanofiltration, and a low pH incubation at elevated temperature (30°C to 32°C). The S/D process includes treatment with an organic mixture of tri-n-butyl phosphate, octoxynol 9 and polysorbate 80 at 18°C to 25°C for a minimum of 60 minutes. S/D treatment inactivates the lipid-enveloped viruses investigated to below detection limits within minutes^13. The ethanol fractionation process provides an additional virus clearance capacity.

In vitro virus spiking studies have been used to validate the capability of the manufacturing process to inactivate and remove viruses. To establish the minimum applicable virus clearance capacity of the manufacturing process, these virus clearance studies were performed under extreme conditions (e.g., at minimum S/D concentrations, incubation time and temperature for the S/D treatment).

Virus clearance studies for CUVITRU performed in accordance with good laboratory practices are summarized in Table 7.

Table 7 Three Dedicated Independent Virus Inactivation/Removal Steps Mean Log10 Reduction Factors [For the calculation of these RF data from virus clearance study reports, applicable manufacturing conditions were used. Log10 RFs on the order of 4 or more are considered effective for virus clearance in accordance with the Committee for Medicinal Products for Human Use (CHMP, formerly CPMP) guidelines.] (RFs) For Each Virus and Manufacturing Step
Virus type | Enveloped RNA |  |  | Enveloped DNA | Non-enveloped RNA |  | Non-enveloped DNA
Family | Retroviridae | Flaviviridae |  | Herpesviridae | Picornaviridae |  | Parvoviridae
Virus | HIV-1 | BVDV | WNV | PRV | HAV | EMCV | MMV
Fractionation | >5.1 | 1.3 | >6.1 | >4.9 | 3.9 | 4.2 | 4.9
SD treatment | >4.5 | >6.2 | n.a. | >4.8 | n.d. | n.d. | n.d
35 nm nanofiltration | >4.5 | >5.1 | >6.2 | >5.6 | 5.7 | 1.4 | 2.0
Low pH treatment | >5.8 | >5.5 | >6.0 | >6.5 | n.d. [No RF obtained due to immediate neutralization of HAV by the anti-HAV antibodies present in the product.] | >6.3 | 3.1
Overall log reduction factor (ORF) | >19.9 | >18.1 | >18.3 | >21.8 | 9.6 | >11.9 | 10.1
Abbreviations: HIV-1, Human Immunodeficiency Virus Type 1; BVDV, Bovine Viral Diarrhea Virus (model for Hepatitis C Virus and other lipid enveloped RNA viruses); WNV, West Nile Virus; PRV, Pseudorabies Virus (model for lipid enveloped DNA viruses, including Hepatitis B Virus); EMCV, Encephalomyocarditis Virus (model for non-lipid enveloped RNA viruses, including Hepatitis A virus [HAV]); MMV, Mice Minute Virus (model for non-lipid enveloped DNA viruses, including B19 virus [B19V]); n.d. (not done), n.a. (not applicable).

12 CLINICAL PHARMACOLOGY

12.1 Mechanism of Action

CUVITRU supplies a broad spectrum of opsonizing and neutralizing IgG antibodies against a wide variety of bacterial and viral agents. CUVITRU also contains a spectrum of antibodies capable of interacting with and altering the activity of cells of the immune system as well as antibodies capable of reacting with cells such as erythrocytes. The role of these antibodies and the mechanisms of action of IgG in CUVITRU have not been fully elucidated.

12.2 Pharmacodynamics

Human normal immunoglobulin contains mainly immunoglobulin G (IgG) with a broad spectrum of antibodies against infectious agents. Human normal immunoglobulin contains the IgG antibodies present in the normal population. It has a distribution of immunoglobulin G subclasses closely proportional to that in native human plasma.

Adequate doses of CUVITRU may restore abnormally low immunoglobulin G levels to the normal range.

12.3 Pharmacokinetics

Pharmacokinetic (PK) parameters of subcutaneously administered CUVITRU were evaluated in 60 subjects with primary immunodeficiency (PI) during a clinical study in North America [see Clinical Studies (14)]. Subjects were treated intravenously for 13 weeks with a comparator product [GAMMAGARD LIQUID, Immune Globulin (Human), 10%] and then switched to weekly subcutaneous CUVITRU infusions. Initially, subjects were treated for up to 12 to 16 weeks at a subcutaneous dose that was 145% of the intravenous dose. A comparison of the area under the curve (AUC) for subcutaneous versus intravenous infusions was performed on 15 subjects aged 12 years and older. Subsequently, all subjects were treated with this dose for 12 weeks after which the dose was individualized for all subjects using the trough IgG levels, as described below. After approximately 4 months treatment at this subcutaneous dose, a PK evaluation was conducted on all subjects.

At this dose adjustment, the geometric mean ratio of the AUC for subcutaneous CUVITRU versus intravenous administration immune globulin 10% was 109%. The peak IgG level occurred at a geometric mean of 79 hours after subcutaneous CUVITRU administration.

In part 4 of the study, pharmacokinetic parameters for CUVITRU were assessed for 60 subjects aged 2 years and older. The pharmacokinetic parameters of CUVITRU administered subcutaneously are shown in Table 8. The median peak IgG levels were lower (1,809 mg/dL) during subcutaneous treatment with CUVITRU compared to IGIV 10% administration (2,602 mg/dL for 3 week intervals and 2,521 mg/dL for 4 week intervals), consistent with the lower weekly dose compared with the dose administered every 3 or 4 weeks intravenously. In contrast, the geometric mean trough levels were higher with CUVITRU (1,474 mg/dL), compared with those when given intravenously (1,158 mg/dL for 3 week intervals and 1,019 mg/dL for 4 week intervals), a result of both higher monthly dose and more frequent dosing. Weekly subcutaneous administration resulted in relatively stable steady-state serum IgG levels compared with IGIV administered at 3 to 4 week intervals. Pharmacokinetic parameters for CUVITRU did not significantly differ between age groups. The pharmacokinetic parameters of CUVITRU for the different age groups are shown in Table 9.

Table 8 Pharmacokinetic Parameters
Parameter | Median (95% Cl) N=60
AUC [g*days/L] | 115 (110 to 121)
Apparent clearance [mL/kg/day] | 1.86 (1.80 to 2.17)
Cmax [mg/dL] | 1,809 (1,745 to 2,068)
Cmin [mg/dL] | 1,477 (1,323 to 1,535)
Tmax [hours] | 105 (71 to 119)

Table 9 Pharmacokinetic Parameters by Age Group
Parameter | Age Groups
 | 2 to <5 (n=1) Median (95% CI) | 5 to <12 (n=10) Median (95% CI) | 12 to <16 (n=5) Median (95% CI) | 16 to <65 (n=37) Median (95% CI) | ≥65 (n=7) Median (95% CI)
AUC [g*days/L] | 106 (N/A) | 110 (87 to 121) | 116 (N/A) | 114 (103 to 127) | 139 (90 to 158)
Apparent clearance [mL/kg/day] | 1.86 (N/A) | 1.85 (1.31 to 2.37) | 1.80 (N/A) | 1.98 (1.81 to 2.23) | 1.72 (0.90 to 2.36)
Cmax [mg/dL] | 1,619 (N/A) | 1,725 (1,518 to 1,892) | 1,732 (N/A) | 1,940 (1,778 to 2,220) | 2,419 (1,480 to 3,201)
Cmin [mg/dL] | 1,527 (N/A) | 1,351 (1,130 to 1,635) | 1,554 (N/A) | 1,423 (1,231 to 1,524) | 1,585 (976 to 2,000)
Tmax [hours] | 70 (N/A) | 164 (70 to 168) | 68 (N/A) | 74 (68 to 119) | 119 (24 to 164)

13 NONCLINICAL TOXICOLOGY

13.1 Carcinogenesis, Mutagenesis, Impairment of Fertility

No animal studies were conducted to evaluate the carcinogenic or mutagenic effects of CUVITRU or its effects on fertility.

13.2 Animal Toxicology and/or Pharmacology

Animal studies were conducted to evaluate possible toxicity of CUVITRU.

In a local tolerance study in mini-pigs, 50 mL of CUVITRU were administered subcutaneously to anesthetized mini-pigs. Subcutaneous administration of CUVITRU was well tolerated in this study.

In local tolerance studies in rabbits, mild to moderate inflammatory reactions were observed locally after subcutaneous administration of 2.5 mL/kg of CUVITRU. These reactions are considered to be a consequence of the animals' immune response to the human IgG preparation and thus model specific and of minor relevance for the assessment of clinical local tolerability.

14 CLINICAL STUDIES

North America Study

A prospective, open-label, non-controlled, multicenter clinical study was conducted in North America to determine the efficacy, tolerability and PK of CUVITRU in 77 adult and pediatric subjects with PI. Efficacy was determined in 53 adults aged 16 years or older, 6 adolescents aged 12 to <16 years, and 15 children aged 2 to <12 years. CUVITRU was administered to 74 subjects with a mean dose of 222 mg/kg/week ± 71 mg/kg/week for a median treatment duration of 380.5 days (range: 30 - 629 days) and a mean (± SD) of 413.1 ± 116.5 days. The median duration of treatment did not vary significantly between age groups. The total exposure to CUVITRU was 83.70 subject-years and 4,327 infusions.

Initially subjects received immune globulin 10% intravenously (IGIV) every 3 or 4 weeks at a monthly dose equivalent to that received prior to the study for 13 weeks. The objective of part 1 of the study was to determine AUCIV of total IgG following IGIV administration. In part 2 of the study, subjects received CUVITRU subcutaneously at an adjusted dose of 145% of the IGIV dose. The objective of part 2 was to determine AUCSC of total IgG following weekly CUVITRU administration and to calculate an adjusted dose to be used in part 3. The dose adjustment factor was assessed to be 145% of the IGIV 10% dose by comparing the AUCSC with the AUCIV, 0-τ (standardized to 1 week) of part 1 for the first 15 subjects that completed part 2. Subjects who completed part 1 after this assessment was available, went directly into part 3. In part 3 of the study, subjects were treated weekly for 12 weeks at the adjusted dose. The ratio of serum IgG trough levels for part 1 and 3 were compared to the expected trough level determined in part 2 to establish the individually adapted dose for part 4 for each subject. In part 4 of the study, subjects were infused weekly with CUVITRU at the individually adapted dose for 40 weeks. During part 4, an additional pharmacokinetic assessment was performed. Follow-up with the subject either by diary system or by investigator occurred 3-5 days after every infusion in each study part to document adverse events. Adverse events were assessed using the subject's eDiary – all subjects received eDiary tablet to continuously record home treatments, adverse events, and additional information as they occurred.

One acute serious bacterial infection (ASBI) of pneumonia was reported in a 78-year old subject who had specific antibody deficiency and allergic bronchopulmonary aspergillosis while receiving CUVITRU. The point estimate of the annualized rate of ASBIs was 0.012 (upper limit of 99% CI: 0.024) during CUVITRU treatment. This annual rate of ASBIs was lower than 1.0 ASBIs /year (p<0.0001), the threshold specified as providing substantial evidence of efficacy.

The summary of infections and associated events for subjects during subcutaneous treatment with CUVITRU is summarized in Table 10.

Table 10 Summary of Infections and Associated Events
Parameters | Results
Number of subjects Total number of subject-years on treatment Annual rate of any infections (per subject-year) | 74 83.70 2.41 (95% CI: 1.89 to 3.03)
Days on antibiotics (rate per subject-year) | 57.59 (95% CI: 40.71 to 78.59)
Days off work/school/unable to perform normal daily activities due to illness or infection (rate per subject-year) | 1.16 (95% CI: 0.70 to 1.79)
Number of hospitalizations due to infections (rate per subject-year) | 0.012 (95% CI: 0.006 to 0.022)
Number of days in hospital due to infections (rate per subject-year) | 0.06 (95% CI: 0.03 to 0.11)

In the clinical study, across all age groups, the median maximum infusion rate was 60 mL/hr/site. This infusion rate was achieved in 57.3% (2,480/4,327) of completed CUVITRU infusions. CUVITRU infusion rate of 60 mL/h/site was achieved in 28.6% (6/21) of pediatric subjects (2 years to <16 years of age), in 88.7% (47/53) of adults (16 years of age and older) and in 71.6% (53/74) of all subject. For more than half of CUVITRU infusions (2,393/4,327), a volume of 30 to 39 mL (1,096/4,327 infusions) or 40 to 49 mL (1,297/4,327 infusions) was infused per site. For 320/4,327 of CUVITRU infusions, a volume of 60 mL/site or more was infused. Infusion parameters resulted in a median of 2 infusion sites (range: 1 to 4) per CUVITRU administration. During CUVITRU treatment, 84.9% (3,662/4,314) of infusions were administered using 1 infusion site (18.5%; 798/4,314) or 2 infusion sites (66.4%; 2,864/4,314) across all ages. The median duration of infusions was less than 1 hour (0.95 h; range: 0.2-6.4 hours). During all treatment periods, 99.8% of infusions were completed without a reduction, interruption, or discontinuation for tolerability reasons. Infusion characteristics did not significantly differ between adult and pediatric subjects.

Throughout the study, health-related quality of life was assessed using the Pediatric Quality of Life Inventory™ (PEDS-QL) questionnaire^14 (pediatric subjects) or the self-administered SF-36 survey^15(adult subjects). Quality of life was analyzed separately for the age groups 2 to 4 and 5 to 7 years (PEDS-QL, observer: parent), 8 to 12 and 13 years (PEDS-QL, observer: subject) and 14 years and older (SF-36, observer: subject). Treatment satisfaction was measured using the Life Quality Index questionnaire (LQI)^16,17 and the Treatment Satisfaction Questionnaire for Medication (TSQM-9)^18. The LQI was assessed for the age group 2 years to 12 years (observer: parent) and the age group 13 years and older (observer: subject) in three domains: Treatment Interference, Therapy-related Problems and Therapy Settings. The TSQM-9 was assessed in subjects aged 2 to 12 years (observer: parent) and 13 years and older (observer: subject) in 3 domains: Effectiveness, Convenience and Global Satisfaction. Differences between scores during the intravenous study part and subcutaneous 20% study part were calculated for selected domains of the instruments, see Table 11.

Table 11 Selected Patient Reported Outcomes: Differences Between the Intravenous and Subcutaneous Treatment
Scale | Difference | p-value
SF-36 Physical Component Score | 0.89 | 0.067
SF-36 Mental Component Score | 1.31 | 0.976
Total Score (PedsQL) | 1.09 | 0.449
Treatment Interference (LQI) | 1.50 | 0.008
Convenience (TSQM-9) | 11.11 | <0.001

European Study

A prospective, open-label, non-controlled, multicenter study conducted in 16 sites in Europe to evaluate the efficacy, safety, tolerability, and PK parameters of CUVITRU in subjects with PI aged 2 years and older at time of screening. The study consisted of 2 parts. In study part 1, subjects were treated with IGSC 16% for 12 weeks or with IGIV 10% for 13 weeks. Administration, dosage frequency, and dose were dependent on the pre-study treatment. However, the dose range had to be within 0.3-1.0 g/kg BW/4 weeks.

During study part 2, subjects received weekly CUVITRU infusions for 51 weeks at the dose used during study part 1, adjusted to a weekly equivalent dose if necessary. PK assessments were performed before the end of study part 1 and after approximately 5 months in study part 2 in subjects aged ≥12 years. For younger subjects (aged 2 to <12 years) only IgG trough levels were assessed to avoid multiple blood draws. The geometric mean of CUVITRU trough levels was 827 mg/dL [95% CI: 748-913]. Human and population PK parameters for CUVITRU were calculated from levels of Immunoglobulin G (IgG) measured during each part of the study.

CUVITRU was administered at the same weekly-equivalent dose as with the previously used IG product (mean (± SD) dose: 0.125 ± 0.042 g/kg/week). CUVITRU administered at this dose was shown to be effective in PI subjects aged ≥2 years.

One acute serious bacterial infection (ASBI) of pneumonia was reported in a 12-year old subject with a more severe form of hypogammaglobulinemia (XLA) while receiving CUVITRU. The point estimate of the annualized rate of ASBIs was 0.022 (upper limit of 99% CI: 0.049) during CUVITRU treatment. This annual rate of ASBIs was lower than 1.0 ASBIs /year, (p<0.0001), the threshold specified as providing substantial evidence of efficacy.

The summary of infections and associated events for subjects in the EU study during subcutaneous treatment with CUVITRU are summarized in Table 12.

Table 12 Summary of Infections and Associated Events
Parameters | Results
Number of subjects Annual rate [Rate = number of infections divided by the total number of subject-years under treatment] of any infections (rate per subject-year) | 48 4.38 (95% CI: 3.38 to 5.56)
Days on antibiotics (rate per subject-year) | 18.11 (95% CI: 13.01 to 24.41)
Days off work/school/unable to perform normal daily activities due to illness or infection (rate per subject-year) | 15.55 (95% CI: 10.06 to 22.75)
Number of hospitalizations due to infections (rate per subject-year) | 0.04 (95% CI: 0.02 to 0.08)
Number of days in hospital due to infections (rate per subject-year) | 0.11 (95% CI: 0.05 to 0.21)

15 REFERENCES

1. Orange JS, Hossny EM, Weiler CR, Ballow M, Berger M, Bonilla FA, Buckley R, Chinen J, El-Gamal Y, Mazer BD, Nelson Jr. RP, Patel DD, Secord E, Sorenson RU, Wasserman RL, Cunningham-Rundles C, Use of Intravenous Immunoglobulin in Human Disease: A Review of Evidence by Members of the Primary Immunodeficiency Committee of the American Academy of Allergy, Asthma, and Immunology. J Allergy Clin Immunol 2006; 117:S525-53.
2. Bonilla FA, Bernstein IL, Khan DA, Ballas ZK, Chinen J, Frank MM, et al. Practice parameter for the diagnosis and management of primary immunodeficiency. Ann Allergy Asthma Immunol. 2005; 94(suppl 1):S1-63.
3. Pierce LR, Jain N. Risks associated with the use of intravenous immunoglobulin. Transfusion Med Rev. 2003;17:241-251.
4. Dantal J. Intravenous immunoglobulins: in-depth review of excipients and acute kidney injury risk. Am J Nephrol. 2013;38(4):275-84.
5. Katz U, Sheonfeld Y. Review: intravenous immunoglobulin therapy and thromboembolic complications. Lupus 2005;14:802-8.
6. Ramírez E, Romero-Garrido JA, López-Granados E, Borobia AM, Pérez T, Medrano N, Rueda C, Tong HY, Herrero A, Frías J. Symptomatic thromboembolic events in patients treated with intravenous-immunoglobulins: results from a retrospective cohort study. Thromb Res. 2014 Jun;133(6):1045-51.
7. Wilson JR, Bhoopalam N, Fisher M. Hemolytic anemia associated with intravenous immunoglobulin. Muscle Nerve 1997;20:1142-1145.
8. Kessary-Shoham H, Levy Y, Shoenfeld Y, Lorber M, Gershon H. In vivo administration of intravenous immunoglobulin (IVIg) can lead to enhanced erythrocyte sequestration. J Autoimmun 1999;13:129-135.
9. Daw Z, Padmore R, Neurath D, Cober N, Tokessy M, Desjardins D, et al. Hemolytic transfusion reactions after administration of intravenous immune (gamma) globulin: a case series analysis. Transfusion. 2008; 48:1598-601.
10. Copelan EA, Strohm PL, Kennedy MS, Tuschka PJ, Hemolysis following intravenous immune globulin therapy. Transfusion 1986;26:410-412.
11. Berg R, Shebl A, Kimber MC, Abraham M, Schreiber GB. Hemolytic events associated with intravenous immune globulin therapy: a qualitative analysis of 263 cases reported to four manufacturers between 2003 and 2012. Transfusion. 2015 Jul;55 Suppl 2:S36-46.
12. Kahwaji J, et al.; Acute hemolysis after High-Dose Intravenous Immunoglobulin Therapy in Highly HLA Sensitized Patients. Clin J Am Soc Nephrol; 2009 (4):1993-97.
13. Kreil TR, Berting A, Kistner O, Kindermann J. West Nile virus and the safety of plasma derivatives: verification of high safety margins, and the validity of predictions based on model virus data. Transfusion 2003;43:1023-1028.
14. Varni JW, Seid M, Rode CA. The PedsQL: measurement model for the pediatric quality of life inventory. Med.Care 1999;37:126-139.
15. Ware JE, Jr., Sherbourne CD. The MOS 36-item short-form health survey (SF-36). I. Conceptual framework and item selection. Med.Care 1992;30:473-483.
16. Daly PB, Evans JH, Kobayashi RH et al. Home-based immunoglobulin infusion therapy: quality of life and patient health perceptions. Ann.Allergy 1991;67:504-510.
17. Nicolay U, Haag S, Eichmann F et al. Measuring treatment satisfaction in patients with primary immunodeficiency diseases receiving lifelong immunoglobulin replacement therapy. Qual.Life Res. 2005;14:1683-1691.
18. Bharmal M, Payne K, Atkinson MJ et al. Validation of an abbreviated treatment satisfaction questionnaire for medication (TSQM-9) among patients on antihypertensive medications. Health Qual.Life Outcomes 2009;7:36.

16 HOW SUPPLIED/STORAGE AND HANDLING

How Supplied

CUVITRU is supplied in single-dose vials containing the labeled amount of functionally active IgG. The components used in the packaging for CUVITRU are not made with natural rubber latex.

The following presentations of CUVITRU are available:

NDC Number | Volume | Grams Protein
0944-2850-01 | 5 mL | 1.0
0944-2850-03 | 10 mL | 2.0
0944-2850-05 | 20 mL | 4.0
0944-2850-07 | 40 mL | 8.0
0944-2850-09 | 50 mL | 10.0

Storage and Handling

- Store at refrigeration temperature: 2°C to 8°C [36°F to 46°F] for up to 36 months or
- Room temperature: not to exceed 25°C [77°F]) for up to 24 months.
- Do not return CUVITRU to the refrigerator if you take it out to room temperature.
- Do not freeze.
- Do not shake.
- Keep the vials in the carton in order to protect from light.
- Discard any unused product.
- Do not use past the expiration date.

17 PATIENT COUNSELING INFORMATION

- Advise patients to read the FDA-approved patient labeling (Information for Patients and Instructions for Use).
- Prior to starting CUVITRU ask about a history of IgA deficiency, allergic reactions to immune globulin or other blood products. Patients with a history of allergic reactions should not be treated subcutaneously at home until several treatments have been administered and tolerated under medical supervision [see Warnings and Precautions (5.1)].
- Inform patients to immediately report the following signs and symptoms to their healthcare provider:
  - Decreased urine output, sudden weight gain, fluid retention/edema, and/or shortness of breath [see Warnings and Precautions (5.2)].
  - Instruct patients to immediately report symptoms of thrombosis. These symptoms may include pain and/or swelling of an arm or leg with warmth over the affected area, discoloration of an arm or leg, unexplained shortness of breath, chest pain or discomfort that worsens on deep breathing, unexplained rapid pulse, numbness or weakness on one side of the body [see Warnings and Precautions (5.3)].
  - Severe headache, neck stiffness, drowsiness, fever, sensitivity to light, painful eye movements, nausea, and vomiting [see Warnings and Precautions (5.4)].
  - Increased heart rate, fatigue, yellowing of the skin or eyes, and dark-colored urine [see Warnings and Precautions (5.5)].
  - Trouble breathing, chest pain, blue lips or extremities, or fever that can occur 1 to 6 hours after an infusion of CUVITRU [see Warnings and Precautions (5.6)].
- Inform patients that CUVITRU is made from human plasma and may contain infectious agents that can cause disease (e.g., viruses and, theoretically, the vCJD agent). The risk of CUVITRU transmitting an infectious agent has been reduced by screening plasma donors for prior exposure, testing donated plasma, and inactivating or removing certain viruses during manufacturing. Patients should report any symptoms that concern them which might be caused by virus infections [see Warnings and Precautions (5.7)]
- Inform patients that CUVITRU can interfere with their immune response to live viral vaccines such as measles, mumps, rubella and varicella, and instruct patients to notify their healthcare professional of this potential interaction when they are receiving vaccinations [see Drug Interactions (7)].

Self-administration – If self-administration is deemed to be appropriate by the physician, clear instructions and training on subcutaneous infusion should be given to the patient/caregiver, and the demonstration of their ability to independently administer subcutaneous infusions should be documented.

- Ensure the patient understands the importance of consistent subcutaneous infusions to maintain appropriate steady IgG levels.
- Inform the patient to start the infusion promptly after drawing CUVITRU into the syringe. Ensure the patient understands that it is suggested to complete the administration within 2 hours due to the potential formation of particles caused by siliconized syringes.
- Instruct the patient to keep a treatment diary/log book. This diary/log book should include information about each infusion such as, the time, date, dose, lot number(s), infusion sites, and any reactions.
- Inform the patient that mild to moderate local infusion-site reactions (e.g., pain, redness and itching) are a common side effect of subcutaneous treatment, but to contact their healthcare professional if a local reaction increases in severity or persists for more than a few days.

Takeda Pharmaceuticals U.S.A., Inc.
Cambridge, MA 02142
U.S. License No. 1898

CUVITRU is a registered trademark of Baxalta Incorporated.
Takeda and are registered trademarks of Takeda Pharmaceutical Company Limited.

©2025 Takeda Pharmaceutical Company Limited. All rights reserved.

CUV350

Information For Patients

CUVITRU® (CUE-vih-troo)
immune globulin subcutaneous (human), 20% solution

subcutaneous administration

Information for Patients

The following summarizes important information about CUVITRU. Please read it carefully before using this medicine. This information does not take the place of talking with your healthcare provider, and it does not include all of the important information about CUVITRU. If you have any questions after reading this, ask your healthcare provider.

What is the most important information I need to know about CUVITRU?

CUVITRU can cause the following serious reactions:

- Severe allergic reactions causing difficulty in breathing or skin rashes
- Decreased kidney function or kidney failure
- Blood clots in the heart, brain, lungs, or elsewhere in the body
- Severe headache, drowsiness, fever, painful eye movements, or nausea and vomiting
- Dark colored urine, swelling, fatigue, or difficulty breathing

What is CUVITRU?

CUVITRU is a ready-to-use, liquid medicine that contains immunoglobulin G (IgG) antibodies, which protect the body against infection. CUVITRU is used to treat patients with primary immunodeficiency diseases (PI).

There are many forms of PI. The most common types of PI result in an inability to make a very important type of protein called antibodies, which help the body fight off infections from bacteria or viruses. CUVITRU is made from human plasma that is donated by healthy people. CUVITRU contains antibodies collected from these healthy people that replace the missing antibodies in PI patients.

Who should not use CUVITRU?

Do not use CUVITRU if you have a known history of a severe allergic reaction to immune globulin or other blood products. If you have such a history, discuss this with your healthcare provider to determine if CUVITRU can be given to you. Tell your healthcare provider if you have a condition called selective (or severe) immunoglobulin A (IgA) deficiency.

How should I use CUVITRU?

CUVITRU is given under the skin (subcutaneously). Most of the time infusions under the skin are given at home by self infusion or by caregivers. Instructions for giving CUVITRU under the skin (subcutaneously) are provided in the Instructions for Use brochure. Only use CUVITRU by yourself after you have been instructed by your healthcare provider.

What should I avoid while taking CUVITRU?

CUVITRU can make vaccines (like measles/mumps/rubella or chickenpox vaccines) not work as well for you. Before you get any vaccines, tell your healthcare provider that you take CUVITRU.

Tell your healthcare provider if you are pregnant, or plan to become pregnant, or if you are nursing.

What are the possible or reasonably likely side effects of CUVITRU?

The following one or more possible reactions may occur at the site of infusion. These generally go away within a few hours, and are less likely after the first few infusions.

- Mild or moderate pain
- Redness
- Itching

The most common side effects with CUVITRU are:

- Headache
- Nausea
- Fatigue
- Diarrhea
- Vomiting

If any of the following problems occur after starting treatment with CUVITRU, stop the infusion immediately and contact your healthcare provider or call emergency services. These could be signs of a serious problem.

- Hives, swelling in the mouth or throat, itching, trouble breathing, wheezing, fainting or dizziness. These could be signs of a serious allergic reaction.
- Bad headache with nausea, vomiting, stiff neck, fever, and sensitivity to light. These could be signs of irritation of the lining around your brain.
- Reduced urination, sudden weight gain, or swelling in your legs. These could be signs of a kidney problem.
- Pain, swelling, warmth, redness, or a lump in your legs or arms. These could be signs of a blood clot.
- Brown or red urine, fast heart rate, yellow skin or eyes. These could be signs of a liver problem or a blood problem.
- Chest pain or trouble breathing, or blue lips or extremities. These could be signs of a serious heart or lung problem.
- Fever over 100°F. This could be a sign of an infection.

These are not all of the possible side effects with CUVITRU. You can ask your healthcare provider for physician's information leaflet. Tell your healthcare provider about any side effect that bothers you or that does not go away.

Whenever giving yourself treatments at home, you should have another responsible person present to help treat side effects or get help if you have a serious adverse reaction occur. Ask your healthcare provider whether you should have rescue medications, such as antihistamines or epinephrine.

How do I store CUVITRU?

Store CUVITRU refrigerated or at room temperature.

- You can store CUVITRU in the refrigerator (36°F to 46°F [2°C to 8°C]) for up to 36 months or
- You can store CUVITRU at room temperature (up to 77°F [25°C]) for up to 24 months.
- Do not return CUVITRU to the refrigerator if you take it out to room temperature.
- Do not freeze.
- Do not shake.
- Check the expiration date on the carton and vial label. Do not use CUVITRU after the expiration date.
- Protect from light. You can use the original CUVITRU containers to protect it from light.

Takeda Pharmaceuticals U.S.A., Inc.
Cambridge, MA 02142
U.S. License No. 1898

CUVITRU is a registered trademark of Baxalta Incorporated.
Takeda and are registered trademarks of Takeda Pharmaceutical Company Limited.

©2025 Takeda Pharmaceutical Company Limited. All rights reserved.

Issue Date: 2/2025

CUV350

Detailed Instructions for Administration for Patients

Do not use CUVITRU at home until you get instructions and training from your healthcare professional.

Prepare CUVITRU vial(s):

- Remove CUVITRU from the box. Allow vials to reach room temperature. This may take up to 90 minutes.
- Do not apply heat or place in microwave.
- Do not shake the vial(s).

1. Check the vial(s):
  - Do not use beyond expiration date.
  - Do not use if the protective cap is missing or broken.
  - Look at the color: it should be clear and colorless to pale yellow or light brown.
  - Do not use if the solution is cloudy or has particles.

2. Gather all supplies
  - Gather all supplies:
    Items include: vial(s) of CUVITRU, infusion supplies: subcutaneous needle set, transfer device(s), syringe(s), sterile tip caps, sterile clear bandage, tape, gauze, sharps container, infusion pump, infusion log.
  - Clean work area.
  - Program the infusion pump according to prescribed infusion rates and manufacturer's instructions.
  - Wash hands thoroughly and allow to dry.
  - Open supplies as shown by your healthcare professional.

3. Prepare the syringe(s):
  - Remove the cap from the vial.
  - Wipe each stopper with a sterile alcohol wipe and allow to dry.
  - Attach a sterile syringe to a vented spike.
  - Insert the vented spike into the center of the IG vial.
  - Turn the vial upside down and pull back on the plunger to pull the IG into the syringe(s).
  - Repeat these steps, if using multiple vials to achieve the desired dose.
  - Start the infusion promptly after drawing CUVITRU into the syringe(s). It is suggested to complete the administration within 2 hours.

If using a sterile needle: Attach a sterile syringe to the sterile needle and pull back the plunger of syringe to fill with air which should equal the amount of the solution you will be taking from the vial. Insert the needle into the center of the stopper, and inject air in. Pull back on the plunger to withdraw the desired volume.

4. Prepare the infusion pump and tubing:
  - Use manufacturer directions for filling the tubing and using the pump.
  - Attach the syringe filled with CUVITRU to the needle set.
  - Point the syringe tip up and gently push the plunger of the syringe to remove the air and fill the needle set up to the needle hub.

5. Prepare the infusion site(s):
  - Select the number of infusion sites based on the volume of the total dose.
  - Choose infusion site(s): upper arms, abdomen, thighs, or lower back.
  - Avoid: bony areas, visible blood vessels, scars and any areas of inflammation (irritation) or infection.
  - Infuse CUVITRU from 1 to 4 infusion sites at the same time.
  - Select sites at least 4 inches apart.
  - Rotate sites between future infusions.
  - Wipe the infusion site(s) with a sterile alcohol wipe beginning at the center of each infusion site and moving outward in circular motion. Allow the infusion site(s) to dry (at least 30 seconds).

6. Insert and secure the subcutaneous needle set:
  - Remove the needle cover. Firmly grasp and pinch at least 1 inch of skin between two fingers.
  - Insert needle with a rapid motion straight into the skin at a 90 degree angle. Tape needle in place with sterile tape (included on transparent dressing).
  - If more than one site is used, repeat the steps.
  - Secure the needle set in place by applying a sterile protective dressing over the site(s).

7. Start the infusion:
  - Follow the manufacturer's instructions to turn pump on and start the infusion.
  - Check infusion site(s) occasionally throughout the infusion.

8. Remove subcutaneous needle(s) from the infusion site(s):
  - Remove the needle set by loosening the tape on all edges.
  - Pull the needle wings straight up and out.
  - Gently press a small piece of gauze over the needle site and cover with a dressing.
  - Throw away the needle(s) into the sharps container.

9. Record the infusion:
  - Remove the peel-off label from the vial(s), which has the product lot number and expiration date, and place the label in your treatment record/infusion log.
  - Write down the date, time, dose, site(s) of infusion (to assist in rotating sites) and any reactions after each infusion.
  - Throw away the disposable supplies, vials, and unused product as recommended by your healthcare professional.

Takeda Pharmaceuticals U.S.A., Inc.
Cambridge, MA 02142
U.S. License No. 1898

CUVITRU is a registered trademark of Baxalta Incorporated.
Takeda and are registered trademarks of Takeda Pharmaceutical Company Limited.

©2025 Takeda Pharmaceutical Company Limited. All rights reserved.

Issue Date: 2/2025

CUV350

PRINCIPAL DISPLAY PANEL - 5 mL Vial Label

NDC: 0944-2850-02

Immune Globulin Subcutaneous (Human) 20%
CUVITRU®
Rx Only

1g
5 mL

Single-Dose Vial
Solution for Subcutaneous Administration
The vial stopper is not made with natural rubber latex.
Refrigeration: 2°C to 8°C (36°F to 46°F) for up to 36 months.
Do not freeze. Room temperature: not to
exceed 25°C (77°F) for up to 24 months.
Discard unused portion.

LE-07-62407

Takeda

PRINCIPAL DISPLAY PANEL - 5 mL Vial Carton

NDC: 0944-2850-01

1g
5 mL

Immune Globulin Subcutaneous
(Human) 20%
CUVITRU®

Solution for Subcutaneous Administration

Single-Dose Vial
Rx Only

Takeda

PRINCIPAL DISPLAY PANEL - 10 mL Vial Label

NDC: 0944-2850-04

Immune Globulin Subcutaneous (Human) 20%
CUVITRU®
Rx Only

2g
10 mL

Single-Dose Vial
Solution for Subcutaneous Administration
The vial stopper is not made with natural rubber
latex. Refrigeration: 2°C to 8°C (36°F to 46°F) for up
to 36 months. Do not freeze. Room temperature:
not to exceed 25°C (77°F) for up to 24 months.
Discard unused portion.

LE-07-62411

Takeda

PRINCIPAL DISPLAY PANEL - 10 mL Vial Carton

NDC: 0944-2850-03

2g
10 mL

Immune Globulin Subcutaneous
(Human) 20%
CUVITRU®

Solution for Subcutaneous Administration

Single-Dose Vial
Rx Only

Takeda

PRINCIPAL DISPLAY PANEL - 20 mL Vial Label

NDC: 0944-2850-06

Immune Globulin Subcutaneous (Human) 20%
CUVITRU®

4g
20 mL

Single-Dose Vial
Solution for Subcutaneous Administration
The vial stopper is not made with natural rubber latex.
Refrigeration: 2°C to 8°C (36°F to 46°F) for up to 36 months. Do not freeze.
Room temperature: not to exceed 25°C (77°F) for up to 24 months.
Discard unused portion.
Takeda Pharmaceuticals U.S.A., Inc.
Cambridge, MA 02142
U.S. License No. 1898
CUVITRU is a registered trademark of Baxalta Incorporated.

Rx Only
LE-07-62413
Takeda

PRINCIPAL DISPLAY PANEL - 20 mL Vial Carton

NDC: 0944-2850-05

4g
20 mL

Immune Globulin Subcutaneous
(Human) 20%
CUVITRU®

Solution for Subcutaneous Administration

Single-Dose Vial
Rx Only

Takeda

PRINCIPAL DISPLAY PANEL - 40 mL Vial Label

NDC: 0944-2850-08

Immune Globulin Subcutaneous (Human) 20%
CUVITRU®
Rx Only

8g
40 mL

Single-Dose Vial
Solution for Subcutaneous Administration
The vial stopper is not made with natural rubber latex.

Refrigeration: 2°C to 8°C (36°F to 46°F) for up to 36 months.
Do not freeze.

Room temperature: not to exceed 25°C (77°F) for up to 24 months.
Discard unused portion.

CUVITRU is a registered trademark of Baxalta Incorporated.

Takeda Pharmaceuticals U.S.A., Inc.
Cambridge, MA 02142
U.S. License No. 1898

LE-07-62415

Takeda

PRINCIPAL DISPLAY PANEL - 40 mL Vial Carton

NDC: 0944-2850-07

8g
40 mL

Immune Globulin Subcutaneous
(Human) 20%
CUVITRU®

Solution for Subcutaneous Administration

Single-Dose Vial

Rx Only

Takeda

PRINCIPAL DISPLAY PANEL - 50 mL Vial Label

NDC: 0944-2850-10

Immune Globulin Subcutaneous (Human) 20%
CUVITRU®
Rx Only

10g
50 mL

Single-Dose Vial
Solution for Subcutaneous Administration
The vial stopper is not made with natural rubber latex.

Refrigeration: 2°C to 8°C (36°F to 46°F) for up to 36 months.
Do not freeze.

Room temperature: not to exceed 25°C (77°F) for up to 24 months.
Discard unused portion.

CUVITRU is a registered trademark of Baxalta Incorporated.

Takeda Pharmaceuticals U.S.A., Inc.
Cambridge, MA 02142
U.S. License No. 1898

LE-07-62417
Takeda

PRINCIPAL DISPLAY PANEL - 50 mL Vial Carton

NDC: 0944-2850-09

10g
50 mL

Immune Globulin Subcutaneous
(Human) 20%
CUVITRU®

Solution for Subcutaneous Administration

Single-Dose Vial
Rx Only

Takeda